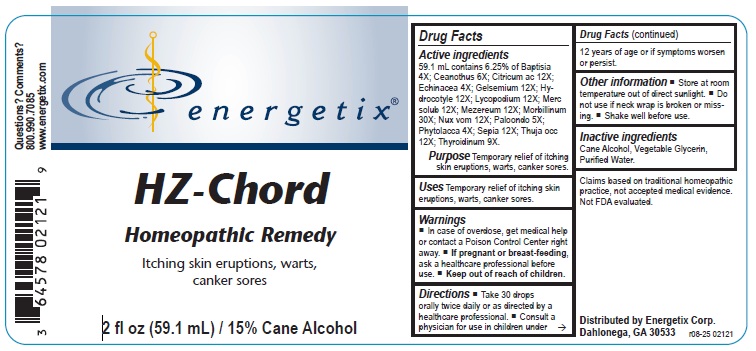 DRUG LABEL: HZ-Chord
NDC: 64578-0065 | Form: LIQUID
Manufacturer: Energetix Corporation
Category: homeopathic | Type: HUMAN OTC DRUG LABEL
Date: 20251217

ACTIVE INGREDIENTS: BAPTISIA TINCTORIA ROOT 4 [hp_X]/1 mL; CEANOTHUS AMERICANUS LEAF 6 [hp_X]/1 mL; ANHYDROUS CITRIC ACID 12 [hp_X]/1 mL; ECHINACEA ANGUSTIFOLIA 4 [hp_X]/1 mL; GELSEMIUM SEMPERVIRENS ROOT 12 [hp_X]/1 mL; CENTELLA ASIATICA 12 [hp_X]/1 mL; LYCOPODIUM CLAVATUM SPORE 12 [hp_X]/1 mL; MERCURIUS SOLUBILIS 12 [hp_X]/1 mL; DAPHNE MEZEREUM BARK 12 [hp_X]/1 mL; MEASLES VIRUS 30 [hp_X]/1 mL; STRYCHNOS NUX-VOMICA SEED 12 [hp_X]/1 mL; LARREA TRIDENTATA TOP 5 [hp_X]/1 mL; PHYTOLACCA AMERICANA ROOT 4 [hp_X]/1 mL; SEPIA OFFICINALIS JUICE 12 [hp_X]/1 mL; THUJA OCCIDENTALIS LEAFY TWIG 12 [hp_X]/1 mL; THYROID, BOVINE 9 [hp_X]/1 mL
INACTIVE INGREDIENTS: WATER; GLYCERIN; ALCOHOL

HZ-Chord

Active ingredients

59.1 mL contains 6.25% of Baptisia 4X; Ceanothus 6X; Citricum ac 12X; Echinacea 4X; Gelsemium 12X; Hydrocotyle 12X; Lycopodium 12X; Merc solub 12X; Mezereum 12X; Morbillinum 30X; Nux vom 12X; Paloondo 5X; Phytolacca 4X; Sepia 12X; Thuja occ 12X; Thyroidinum 9X.

Claims based on traditional homeopathic practice, not accepted medical evidence. Not FDA evaluated.

INDICATIONS AND USAGE

Purpose Temporary relief of itching skin eruptions, warts, canker sores.

Warnings

- In case of overdose, get medical help or contact a Poison Control Center right away.
- If pregnant or breast feeding,ask a health professional before use.

- Keep out of reach of children.

DOSAGE AND ADMINISTRATION

Direcrions

- Take 30 drops orally twice daily or as directed by a healthcare professional.
- Consult a physician for use in children under 12 years of age or if symptoms worsen or persist.

Other information

- Store at room temperature out of direct sunlight.
- Do not use if neck wrap is broken or missing.
- Shake well before use.

Inactive ingredients Cane Alcohol, Vegetable Glycerin, Purified Water

QUESTIONS

Distributed by Energetix Corp.
Dahlonega, GA 30533

Questions? Comments?
800.990.7085
www.energetix.com

PACKAGE LABEL

energetix
HZ-Chord
Homeopathic Remedy
Itching skin eruptions, warts, blisters, canker sores.
2 fl oz (59.1 mL) / 15% Cane Alcohol

PURPOSE

Purpose Temporary relief of itching skin eruptions, warts, canker sores.